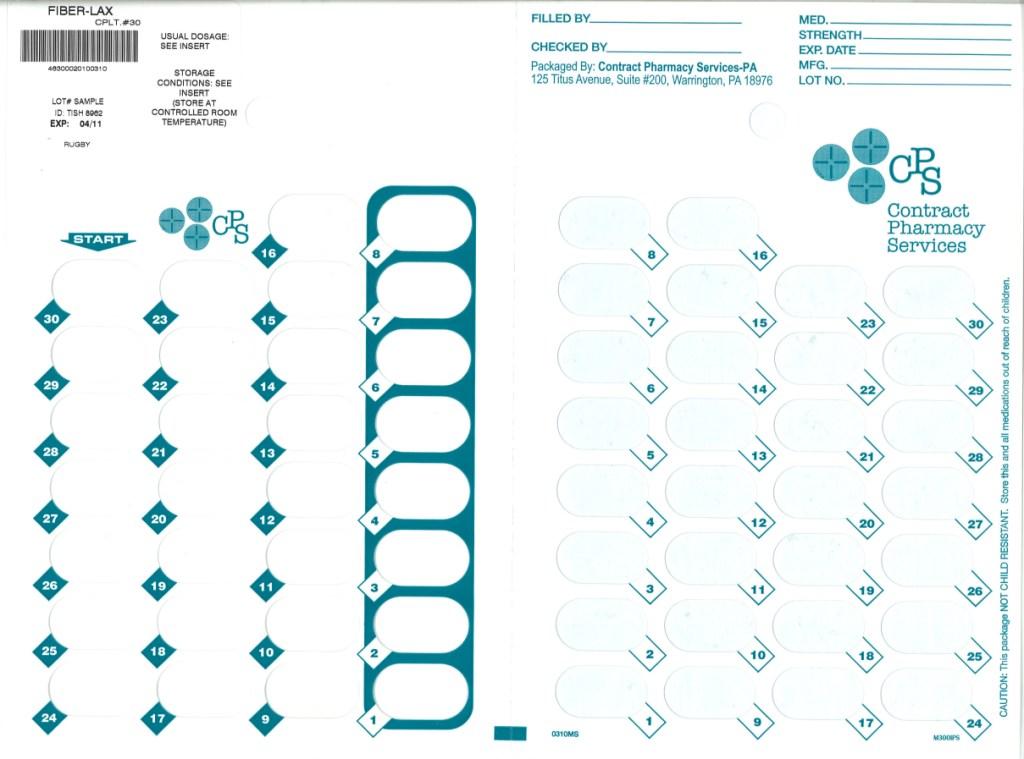 DRUG LABEL: Fiber Lax
NDC: 67046-205 | Form: TABLET
Manufacturer: Contract Pharmacy Services-PA
Category: otc | Type: HUMAN OTC DRUG LABEL
Date: 20100730

ACTIVE INGREDIENTS: CALCIUM POLYCARBOPHIL 500 mg/1 1

Fiber-Lax

ACTIVE INGREDIENT (IN EACH TABLET)

Calcium Polycarbophil 625mg (equivalent to polycarbophil 500mg)

PURPOSE

Bulk-Forming Laxative

USES

- relieves occasional constipation

- generally produces bowel movement in 12 to 72 hours

WARNINGS

Choking: Taking this product without adequate fluid may cause it to swell and block your throat or esophagus and may cause choking. Do not take this product if you have difficulty in swallowing. If you experience chest pain, vomiting, or difficulty in swallowing or breathing after taking this product, seek immediate attention.

Do not use

for longer than one week

Ask a doctor before use if you have

-abdominal pain, nausea, or vomiting

-noticed a sudden change in bowel habits that lasts over two weeks

Ask a doctor or pharmacist before use if

you are taking any other drug. Take Fiber-Lax two or more hours before or after other drugs. Laxatives may affect how other drugs work.

Stop use and ask a doctor if

-you have rectal bleeding

-you fail to have a bowel movement after using this product. These may indicate a serious condition.

Keep out of reach of children. In case of overdose, get medical help or contact a Poison Center right away.

DIRECTIONS

Take Fiber-Lax with at least 8 ounces (a full glass) of water or other fluid. Taking this product without enough liquid may cause choking. See choking warning.

-take dose 1-4 times daily - do not take more than 4 doses in 24 hours.

-adults & children 12 years and over: 2 captabs

-children under 12 years: ask a doctor

OTHER INFORMATION

each captab contains: calcium 140mg

STORAGE

-store below 30 degrees C (86 degrees F)

-do not refrigerate

-protect from humidity

INACTIVE INGREDIENTS

Anhydrous lactose, caramel powder, colloidal silicon dioxide, hypromellose, magnesium stearate, microcrystalline cellulose, polyethylene glycol, sodium lauryl and stearic acid.

QUESTIONS OR COMMENTS?

Questions and Comments?

Call 1-800-645-2158, 9am - 5pm ET, Monday - Friday

Repackaged by:
Contract Pharmacy Services-PA
125 Titus Ave Suite 200
Warrington, PA 18976 USA

Original--08/2010--NJW

Package Label

Blister of 30